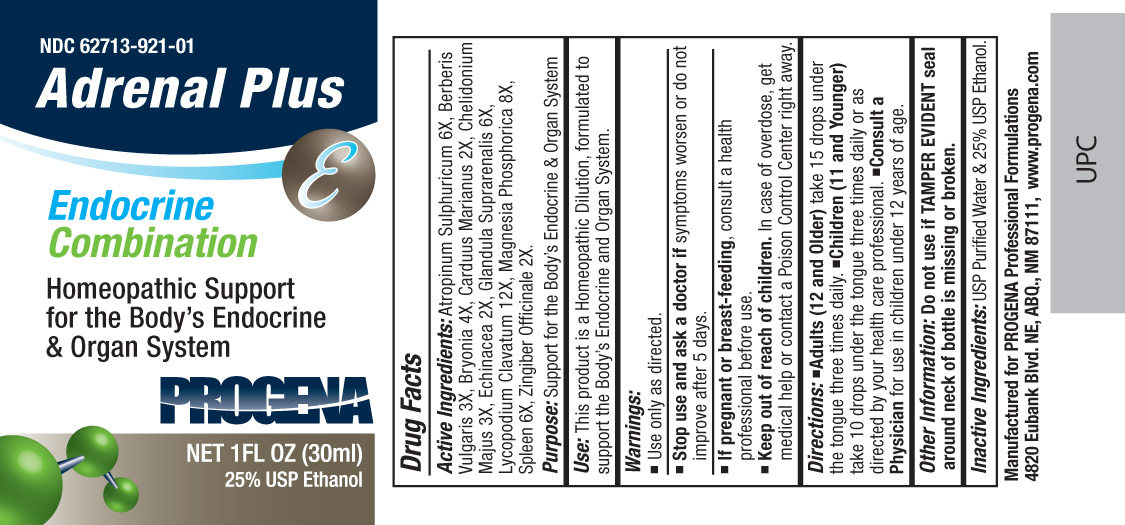 DRUG LABEL: Progena
NDC: 62713-921 | Form: LIQUID
Manufacturer: Meditrend, Inc. DBA Progena Professional Formulations
Category: homeopathic | Type: HUMAN OTC DRUG LABEL
Date: 20130117

ACTIVE INGREDIENTS: ATROPINE SULFATE 6 [hp_X]/1 mL; BERBERIS VULGARIS ROOT BARK 3 [hp_X]/1 mL; BRYONIA ALBA ROOT 4 [hp_X]/1 mL; SILYBUM MARIANUM SEED 2 [hp_X]/1 mL; CHELIDONIUM MAJUS 3 [hp_X]/1 mL; ECHINACEA, UNSPECIFIED 2 [hp_X]/1 mL; SUS SCROFA ADRENAL GLAND 6 [hp_X]/1 mL; LYCOPODIUM CLAVATUM SPORE 12 [hp_X]/1 mL; MAGNESIUM PHOSPHATE, DIBASIC TRIHYDRATE 8 [hp_X]/1 mL; SUS SCROFA SPLEEN 6 [hp_X]/1 mL; GINGER 2 [hp_X]/1 mL
INACTIVE INGREDIENTS: WATER; ALCOHOL

Adrenal Plus

ACTIVE INGREDIENT

Active Ingredients: Atropinum Sulphuricum 6X, Berberis Vulgaris 3X, Bryonia 4X, Carduus Marianus 2X, Chelidonium Majus 3X, Echinacea 2X, Glandula Suprarenalis 6X, Lycopodium Clavatum 12X, Magnesia Phosphorica 8X, Spleen 6X, Zingiber Officinale 2X.

PURPOSE

Purpose: Support for the Body's Endocrine and Organ System

INDICATIONS AND USAGE

Use: This product is a Homeopathic Dilution, formulated to support the Body's Endocrine and Organ System.

Keep Out of Reach of Children. In case of overdose, get medical help or contact a
Poison Control Center right away.

Warnings:

- Use Only as directed.
- Stop use and ask a doctor ifsymptoms worsen or do not improve after 5 days.
- If pregnant or breast-feeding, consult a health professional before use.

DOSAGE AND ADMINISTRATION

Directions:•Adults (12 and Older) take 15 drops under the tongue three times daily.•Children (11 and Younger) take 10 drops under the tongue three times daily or as directed by your health care professional.•Consult a Physicianfor use in children under 12 years of age.

Other Information: Do not use if TAMPER EVIDENT seal around neck of bottle is missing or broken.

Inactive Ingredients: Demineralized water and 25% USP Ethanol.

PACKAGE LABEL

Manufactured for Progena Professional Formulations
4820 Eubank Blvd. NE, ABQ, NM 87111, www.progena.com